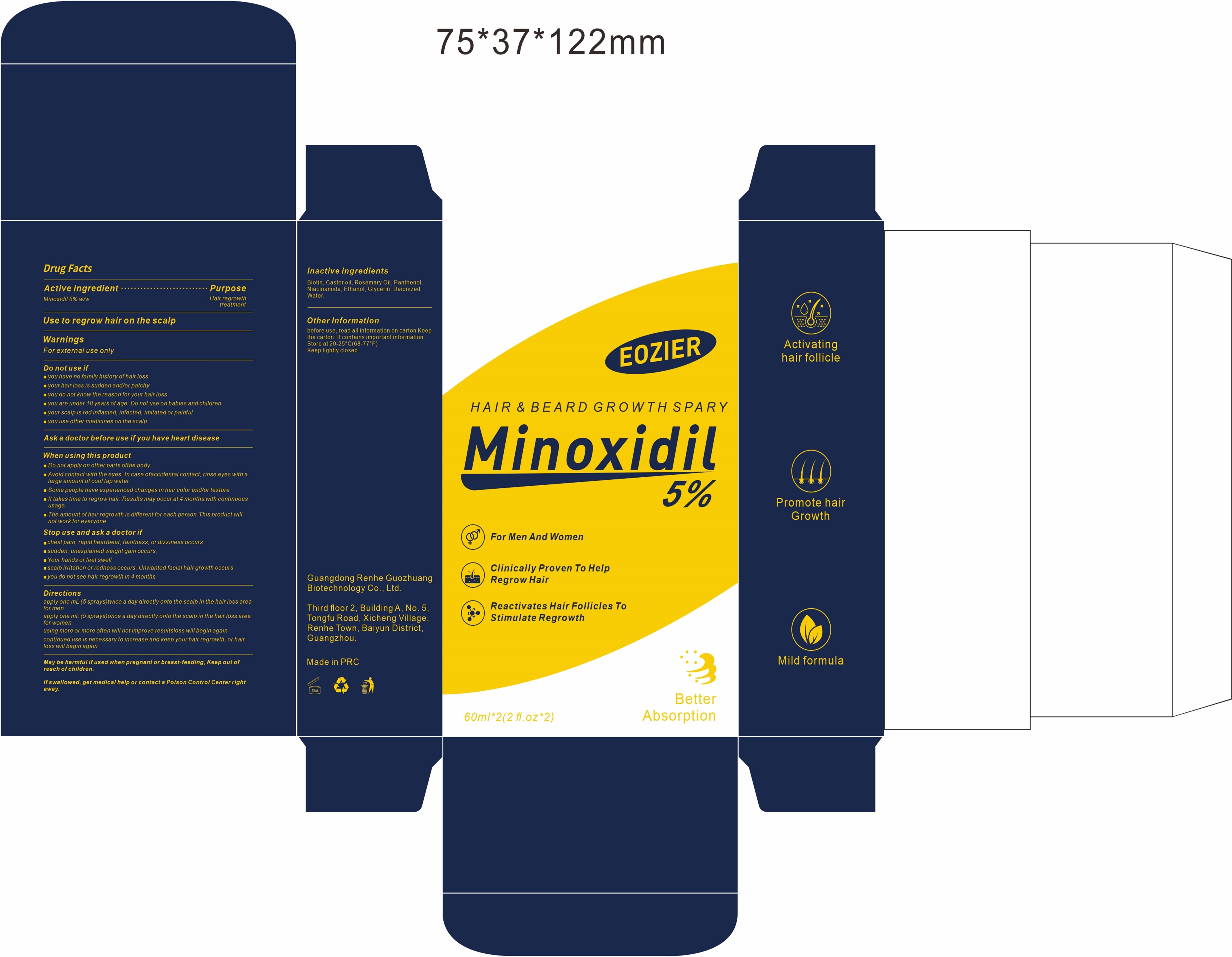 DRUG LABEL: WEST MONTH Botox Stock Solution Anti Aging Serum
NDC: 85435-001 | Form: SOLUTION
Manufacturer: Guangdong Renhe Guozhuang Biotechnology Co., Ltd
Category: otc | Type: HUMAN OTC DRUG LABEL
Date: 20250318

ACTIVE INGREDIENTS: MINOXIDIL 5 mg/100 mg
INACTIVE INGREDIENTS: ROSEMARY OIL 0.1 mg/100 mg; ALOE VERA LEAF 0.1 mg/100 mg; NIACINAMIDE 0.1 mg/100 mg; BIOTIN 0.1 mg/100 mg; PANTHENOL 0.1 mg/100 mg; WATER 5 mg/100 mg; ALCOHOL 44.5 mg/100 mg; GLYCERIN 45 mg/100 mg

ACTIVE INGREDIENT

Minoxidil 5%w/w

PURPOSE

Hair regrowth treatment

INDICATIONS AND USAGE

Use to regrow hair on the scalp

WARNINGS

For external use only

Do not use if

1.you have no family history of hair loss

2.your hair loss is sudden and/or patchy

3.you do not know the reason for your hair loss

4.you are under 18 years of age. Do not use on babies and children

5.your scalp is red infamed,infected, imitated or painful

6.you use other medicines on the scalp

When using this product

1.Do not apply on other parts of the body

2.Avoid contact with the eyes. In case of accidental contact, rinse eyes with large amount of cool tap water

3.Some people have experienced changes in hair color and/or texture

4.It takes time to regrow hair. Results mayoccur at 4 months with continuous usage.

5.The amount ofhair regrowth is different for each person. This product will not work for everyone

STOP USE

1.chest pain, rapid heartbeat, faintness, or dizziness occurs

2.sudden, unexpiained weight gain occurs, Your hands or feet swell

3.scalp irritation or redness occurs. Unwanted facial hair growth occurs

4.you do not see hair regrowth in 4 months

KEEP OUT OF REACH OF CHILDREN

May be harmful if used when pregnant or breast-feeding, Keep out of reach ofchildren.

If swallowed, get medical help or contact a Poison Control Center right away.

Directions

apply one mL (5 sprays)twice a day directly onto the scalp in the hair loss area for men

apply one mL (5 sprays)once a day directly onto the scalp in the hair loss area for women

using more or more often will not improve results

continued use is necessary to increase and keep your hair regrowth, or hair loss will begin again

STORAGE AND HANDLING

before use,read all information on carton

Keep the carton, lt contains important information

Store at 20-25°C(68-77°F)

Keep tightly closed.

INACTIVE INGREDIENT

Biotin,Castor oil, Rosemary Oil, Panthenol,Niacinamide,Ethanol,Glycerin,Deionized Water.